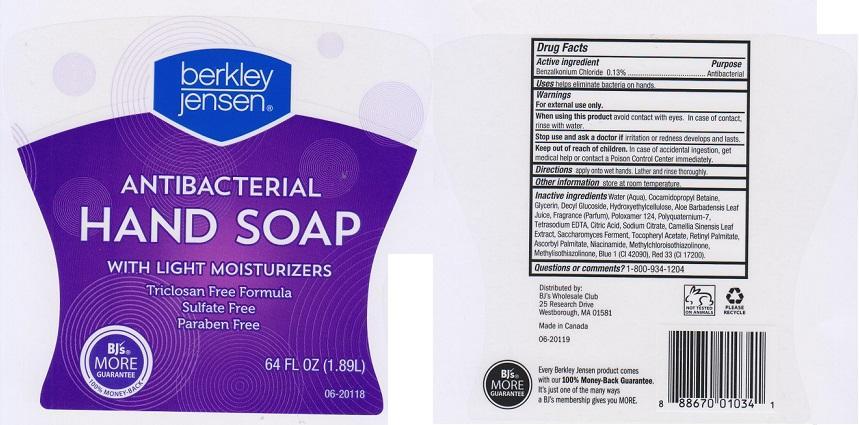 DRUG LABEL: BERKLEY JENSEN
NDC: 68391-150 | Form: LIQUID
Manufacturer: BJWC
Category: otc | Type: HUMAN OTC DRUG LABEL
Date: 20141210

ACTIVE INGREDIENTS: BENZALKONIUM CHLORIDE 1.3 mg/1 mL
INACTIVE INGREDIENTS: WATER; COCAMIDOPROPYL BETAINE; GLYCERIN; DECYL GLUCOSIDE; HYPROMELLOSES; ALOE VERA LEAF; POLOXAMER 124; POLYQUATERNIUM-7 (70/30 ACRYLAMIDE/DADMAC; 1600000 MW); EDETATE SODIUM; CITRIC ACID MONOHYDRATE; SODIUM CITRATE; GREEN TEA LEAF; .ALPHA.-TOCOPHEROL ACETATE; VITAMIN A PALMITATE; ASCORBYL PALMITATE; NIACINAMIDE; METHYLCHLOROISOTHIAZOLINONE; METHYLISOTHIAZOLINONE; FD&C BLUE NO. 1; D&C RED NO. 33

DRUG FACTS

ACTIVE INGREDIENT

BENZALKONIUM CHLORIDE 0.13%

PURPOSES

ANTIBACTERIAL

USES

HELPS ELIMINATE BACTERIA ON HANDS

WARNINGS

FOR EXTERNAL USE ONLY

WHEN USING THIS PRODUCT

AVOID CONTACT WITH EYES. IN CASE OF CONTACT, RINSE WITH WATER

STOP USE AND ASK A DOCTOR IF

IRRITATION OR REDNESS DEVELOPS AND LASTS

KEEP OUT OF REACH OF CHILDREN

IN CASE OF ACCIDENTAL INGESTION, GET MEDICAL HELP OR CONTACT A POISON CONTROL CENTER IMMEDIATELY

DIRECTIONS

APPLY ONTO WET HANDS. LATHER AND RINSE THOROUGHLY

OTHER INFORMATION

STORE AT ROOM TEMPERATURE

INACTIVE INGREDIENTS

WATER (AQUA), COCAMIDOPROPYL BETAINE, GLYCERIN, DECYL GLUCOSIDE, HYDROXYETHYLCELLULOSE, ALOE BARBADENSIS LEAF JUICE, FRAGRANCE (PARFUM), POLOXAMER 124, POLYQUATERNIUM-7, TETRASODIUM EDTA, CITRIC ACID, SODIUM CITRATE, CAMELLIA SINENSIS LEAF EXTRACT, SACCHAROMYCES FERMENT, TOCOPHERYL ACETATE, RETINYL PALMITATE, ASCORBYL PALMITATE, NIACINAMIDE, METHYLCHLOROISOTHIAZOLINONE, METHYLISOTHIAZOLINONE, BLUE 1 (CI 42090), RED 33 (CI 17200)

QUESTIONS OR COMMENTS?

1-800-934-1204